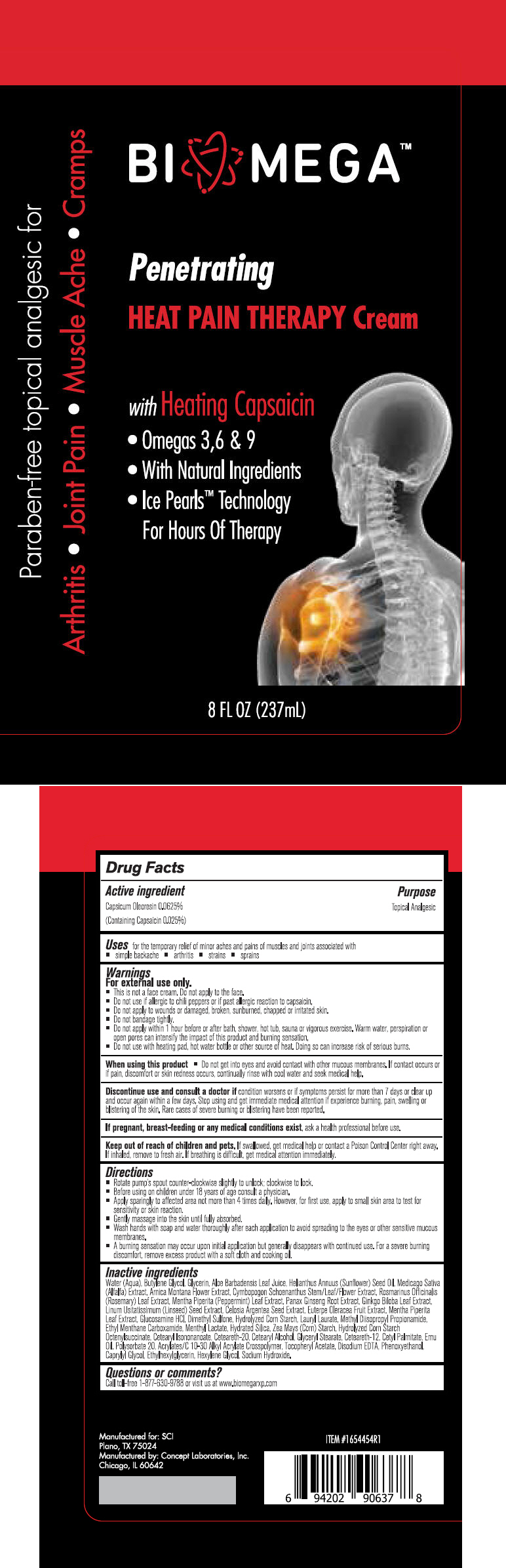 DRUG LABEL: BioMega
NDC: 64058-355 | Form: CREAM
Manufacturer: Concept Laboratories, Inc.
Category: otc | Type: HUMAN OTC DRUG LABEL
Date: 20160921

ACTIVE INGREDIENTS: Capsaicin 2.5 mg/1 g
INACTIVE INGREDIENTS: Water; ALOE VERA LEAF; METHYL DIISOPROPYL PROPIONAMIDE; ETHYL MENTHANE CARBOXAMIDE; MENTHYL LACTATE, (-)-; LAURYL LAURATE; STARCH, CORN; HYDRATED SILICA; GLUCOSAMINE HYDROCHLORIDE; DIMETHYL SULFONE; GLYCERIN; SUNFLOWER OIL; ALFALFA; ARNICA MONTANA FLOWER; CYMBOPOGON SCHOENANTHUS TOP; ROSEMARY; MENTHA PIPERITA LEAF; ASIAN GINSENG; GINKGO; FLAX SEED; CELOSIA ARGENTEA SEED; ACAI; EDETATE DISODIUM; EMU OIL; POLYSORBATE 20; .ALPHA.-TOCOPHEROL ACETATE; BUTYLENE GLYCOL; PHENOXYETHANOL; CAPRYLYL GLYCOL; Ethylhexylglycerin; Hexylene Glycol; CETEARYL ISONONANOATE; POLYOXYL 20 CETOSTEARYL ETHER; CETOSTEARYL ALCOHOL; GLYCERYL MONOSTEARATE; CETEARETH-12; CETYL PALMITATE; SODIUM HYDROXIDE

BioMega™

Drug Facts

Active ingredient

Capsicum Oleoresin 0.0625%

(Containing Capsaicin 0.025%)

Purpose

Topical Analgesic

Uses

for the temporary relief of minor aches and pains of muscles and joints associated with

- simple backache
- arthritis
- strains
- sprains

Warnings

For external use only.

DO NOT USE

- This is not a face cream. Do not apply to the face.
- Do not use if allergic to chili peppers or if past allergic reaction to capsaicin.
- Do not apply to wounds or damaged, broken, sunburned, chapped or irritated skin.
- Do not bandage tightly.
- Do not apply within 1 hour before or after bath, shower, hot tub, sauna or vigorous exercise. Warm water, perspiration or open pores can intensify the impact of this product and burning sensation.
- Do not use with heating pad, hot water bottle or other source of heat Doing so can increase risk of serious burns.

When using this product

- Do not get into eyes and avoid contact with other mucous membranes. If contact occurs or if pain, discomfort or skin redness occurs, continually rinse with cool water and seek medical help.

STOP USE

Discontinue use and consult a doctor if condition worsens or if symptoms persist for more than 7 days or clear up and occur again within a few days. Stop using and get immediate medical attention if experience burning, pain, swelling or blistering of the skin. Rare cases of severe burning or blistering have been reported.

PREGNANCY OR BREAST FEEDING

If pregnant, breast-feeding or any medical conditions exist ask a health professional before use.

Keep out of reach of children and pets. If swallowed, get medical help or contact a Poison Control Center right away. If inhaled, remove to fresh air. If breathing is difficult get medical attention immediately.

Directions

- Rotate pump's spout counter-clockwise slightly to unlock; clockwise to lock.
- Before using on children under 18 years of age consult a physician.
- Apply sparingly to affected area not more than 4 times daily. However, for first use, apply to small skin area to test for sensitivity or skin reaction.
- Gently massage into the skin until fully absorbed.
- Wash hands with soap and water thoroughly after each application to avoid spreading to the eyes or other sensitive mucous membranes.
- A burning sensation may occur upon initial application but generally disappears with continued use. For a severe burning discomfort remove excess product with a soft cloth and cooking oil.

Inactive ingredients

Water (Aqua), Butylene Glycol, Glycerin, Aloe Barbadensis Leaf Juice, Helianthus Annuus (Sunflower) Seed Oil, Medicago Sativa (Alfalfa) Extract, Arnica Montana Flower Extract, Cymbopogon Schoenanthus Stem/Leaf/Flower Extract, Rosmarinus Officinalis (Rosemary) Leaf Extract, Mentha Piperita (Peppermint) Leaf Extract, Panax Ginseng Root Extract, Ginkgo Biloba Leaf Extract, Linum Usitatissimum (Linseed) Seed Extract, Celosia Argentea Seed Extract, Euterpe Oleracea Fruit Extract, Mentha Piperita Leaf Extract, Glucosamine HCl, Dimethyl Sulfone, Hydrolyzed Corn Starch, Lauryl Laurate, Methyl Diisopropyl Propionamide, Ethyl Menthane Carboxamide, Menthyl Lactate, Hydrated Silica, Zea Mays (Corn) Starch, Hydrolyzed Corn Starch Octenylsuccinate, Cetearyl Isononanoate, Ceteareth-20, Cetearyl Alcohol, Glyceryl Stearate, Ceteareth-12, Cetyl Palmitate, Emu Oil, Polysorbate 20, Acrylates/C 10-30 Alkyl Acrylate Crosspolymer, Tocopheryl Acetate, Disodium EDTA, Phenoxyethanol, Caprylyl Glycol, Ethylhexylglycerin, Hexylene Glycol, Sodium Hydroxide.

Questions or comments?

Call toll-free 1-877-630-9788 or visit us at www.biomegard.com

Manufactured for SCI Plano, TX 75024

Manufactured by: Concept Laboratories, Inc. Chicago, IL 60642

PRINCIPAL DISPLAY PANEL - 237 mL Bottle Label

BIOMEGA™

Penetrating
HEAT PAIN THERAPY Cream

with Heating Capsaicin

- Omegas 3,6 & 9
- With Natural Ingredients
- Ice Pearls™ Technology
  For Hours Of Therapy

Paraben-free topical analgesic for

Arthritis • Joint Pain • Muscle Ache • Cramps